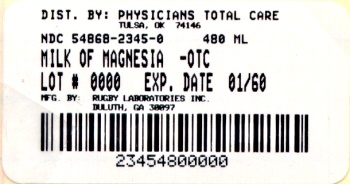 DRUG LABEL: Milk of Magnesia
NDC: 54868-2345 | Form: SUSPENSION
Manufacturer: Physicians Total Care, Inc.
Category: otc | Type: HUMAN OTC DRUG LABEL
Date: 20120124

ACTIVE INGREDIENTS: MAGNESIUM HYDROXIDE 1200 mg/15 mL
INACTIVE INGREDIENTS: water; SODIUM HYPOCHLORITE; SACCHARIN SODIUM

Drug Facts

Active Ingredients

Magnesium hydroxide 1200 mg

Purpose

Saline laxative

Uses

- relieves occasional constipation (irregularity)

- usually produces bowel movement in 1/2 to 6 hours

Warnings

Ask a doctor before use if you have • kidney disease • a magnesium restricted diet
• stomach pain, nausea or vomiting • a sudden change in bowel habits that lasts over 14 days

Ask a doctor or pharmacist before use if you are

taking any other drug. Take this product 2 or more hours before or after other drugs. Laxatives may affect how other drugs work.

Stop use and ask a doctor if

- you have rectal bleeding or no bowel movement after using this product. These could be signs of a serious condition.

- you need to use a laxative for more than 1 week

If pregnant or breast-feeding

ask a health professional before use.

Keep this and all drugs out of the reach of children

In case of accidental overdose, get medical help or contact a Poison Control Center right away.

Directions

- shake well before use

- do not exceed the maximum recommended daily dose in a 24 hour period

- dose may be taken once a day, in divided doses, or as directed by a doctor

- drink a full glass (8oz) of liquid with each dose

adults and children 12 years and older | 2 to 4 tabletspoonfuls (TBSP)
children 6 to 11 years | 1 to 2 tablespoonfuls (TBSP)
children under 6 years | ask a doctor

Other information

- each 15 mL tablespoonful contains: magnesium 500 mg

- store at room temperature and avoid freezing

- close cap tightly after use

- TAMPER-EVIDENT: Do not use if imprinted neckband is missing or broken.

Inactive Ingredients

flavor, purified water, saccharin sodium, sodium hypochlorite

Principal Display Panel

Compare to
Active Ingredient in
Phillips Milk of Magnesia
Rugby Milk of Magnesia is distributed by
Rugby Laboratories, Inc.
Duluth, GA 30097
Additional barcode labeling by;
Physicians Total Care, Inc.
Tulsa, Oklahoma 74146
Milk of Magnesia
Magnesium Hydroxide 1200mg
Saline Laxative
Mint Flavor
Net Contents
16 fl oz (473 mL)